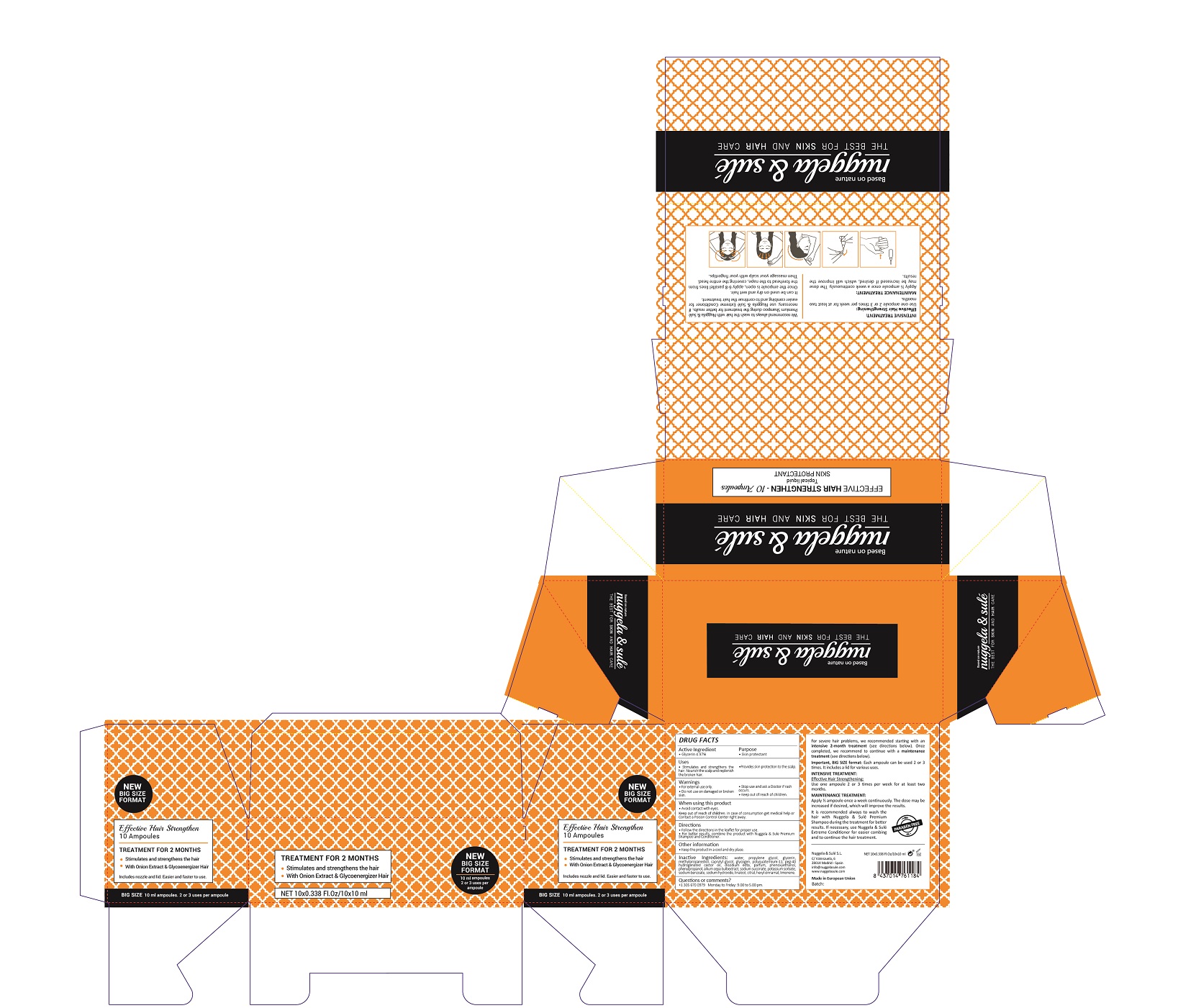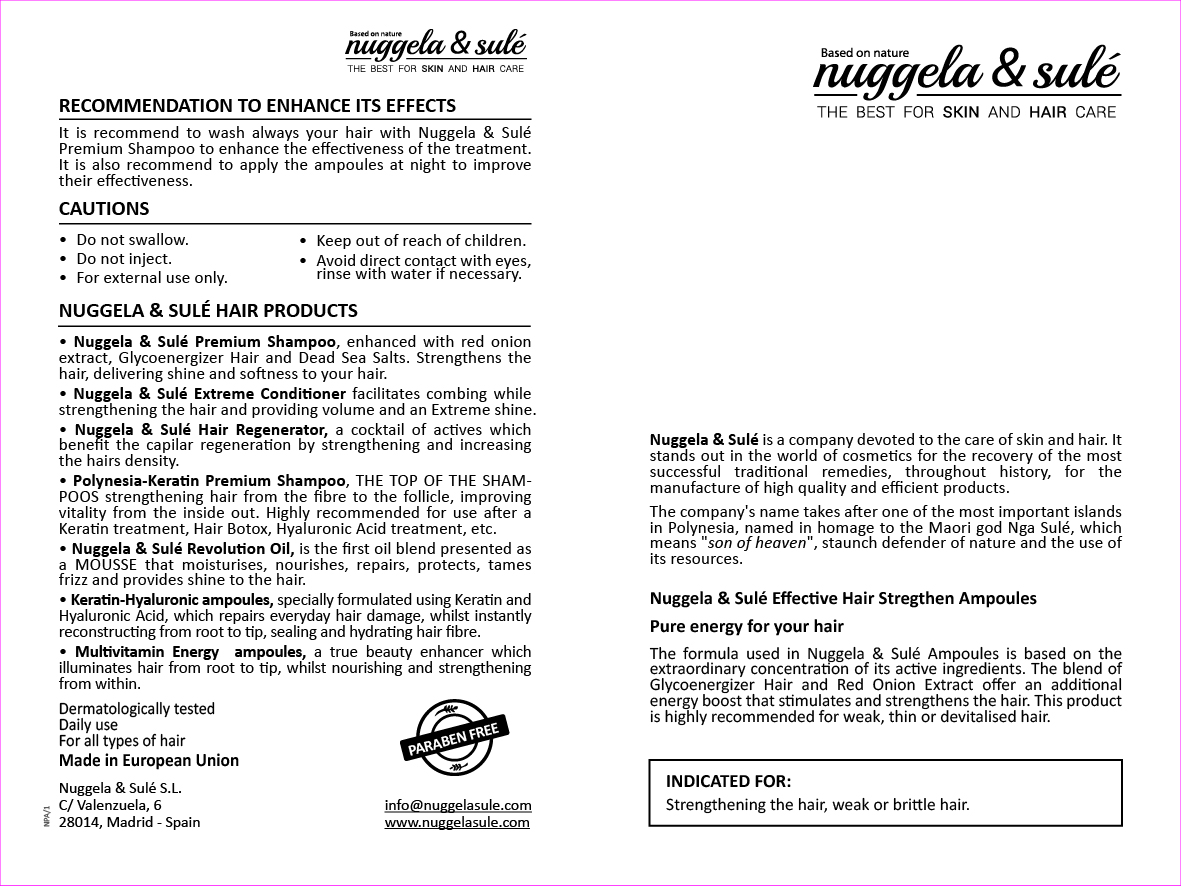 DRUG LABEL: Effective Hair Strengthen
NDC: 71578-003 | Form: SOLUTION
Manufacturer: NUGGELA & SULE SL
Category: otc | Type: HUMAN OTC DRUG LABEL
Date: 20200528

ACTIVE INGREDIENTS: GLYCERIN 4.97 mg/1 mL
INACTIVE INGREDIENTS: LIMONENE, (+)- 0.0001 mg/1 mL; CITRAL 0.0001 mg/1 mL; LINALOOL, (-)- 0.0001 mg/1 mL; WATER 84.31 mg/1 mL; CAPRYLYL GLYCOL 0.52 mg/1 mL; PHENOXYETHANOL 0.15 mg/1 mL; GLYCOGEN 0.5 mg/1 mL; POLYQUATERNIUM-11 (1000000 MW) 0.4 mg/1 mL; PEG-40 CASTOR OIL 0.25 mg/1 mL; EDETATE DISODIUM 0.2 mg/1 mL; PROPANEDIOL 6 mg/1 mL; PHENYLPROPANOL 0.07 mg/1 mL; ONION 0.04 mg/1 mL; POTASSIUM SORBATE 0.005 mg/1 mL; SODIUM BENZOATE 0.005 mg/1 mL; .ALPHA.-HEXYLCINNAMALDEHYDE 0.0001 mg/1 mL; SODIUM SUCCINATE HEXAHYDRATE 0.01 mg/1 mL; SODIUM HYDROXIDE 0.004 mg/1 mL; METHYLPROPANEDIOL 2.4 mg/1 mL

Effective Hair Strengthen topical solution

ACTIVE INGREDIENTS PURPOSE

Glycerin 4.97%.................... Skin Protectant

Warnings

For external use only.

Do not use on damaged or broken skin.

Stop use and ask a doctor if rash occurs.

Keep out of reach of children.

Whhen using this product do not get into eyes.

Children under 6 months: as a doctor.

WARNINGS

Stop use and ask a doctor if rash occurs

Children under 6 months: ask a doctor

Warnings

Keep out of reach of children

Questions or comments?

+ 305 670 0979 M-F 9:00 am to 5:00 pm

Other Information

. keep the product in a cool and dry place

Directions

- follow the directions in the leaflet for proper use
- for better results, combine this product with Nuggela & Sule Premium shampoo and Conditioner

DOSAGE AND ADMINISTRATION

- follow the directions in the leaflet for proper use
- for better results, combine this product with Nuggela & Sule Premium shampoo and Conditioner

Uses

- regenerates and stimulates the hair
- nourish the scalp and provides the needed strenght to the broken and damaged hair
- provides skin protection to the scalp

Inactive Ingredients

AQUA, PROPYLENE GLYCOL, GLYCERIN, METHYLPROPANEDIOL, CAPRYLYL GLYCOL, GLYCOGEN, POLYQUATERNIUM-11, PEG-40 HYDROGENATED CASTOR OIL, DISODIUM EDTA , PARFUm, PHENOXYETHANOL, PHENYLPROPANOL, ALLIUM CEPA BULB EXTRACT, SODIUM SUCCINATE, POTASSIUM SORBATE, SODIUM BENZOATE, SODIUM HYDROXIDE, LINALOOL, CITRAL, HEXYL CINNAMAL, LIMONENE

Uses

- regenerates and stimulates the hair
- nourish the scalp and provides the needed strenght to the broken and damaged hair
- provides skin protection to the scalp

Package Label

Treatment for two months

Stimulate and strenghthen the hair

With onion extract and Glycoenergizer hair